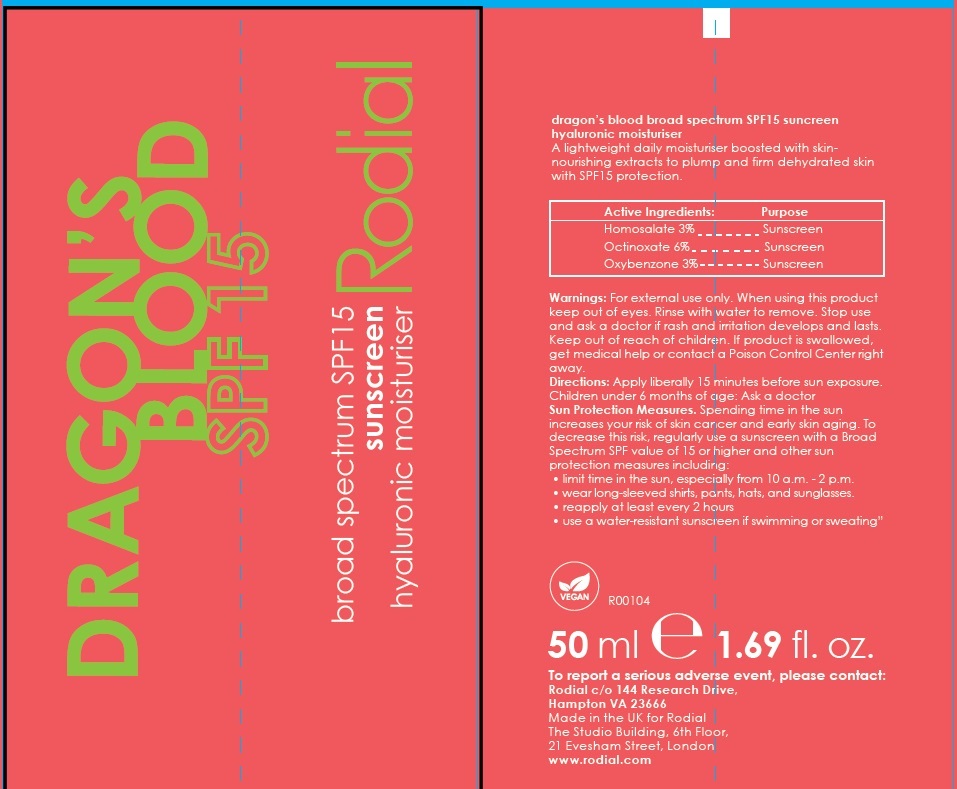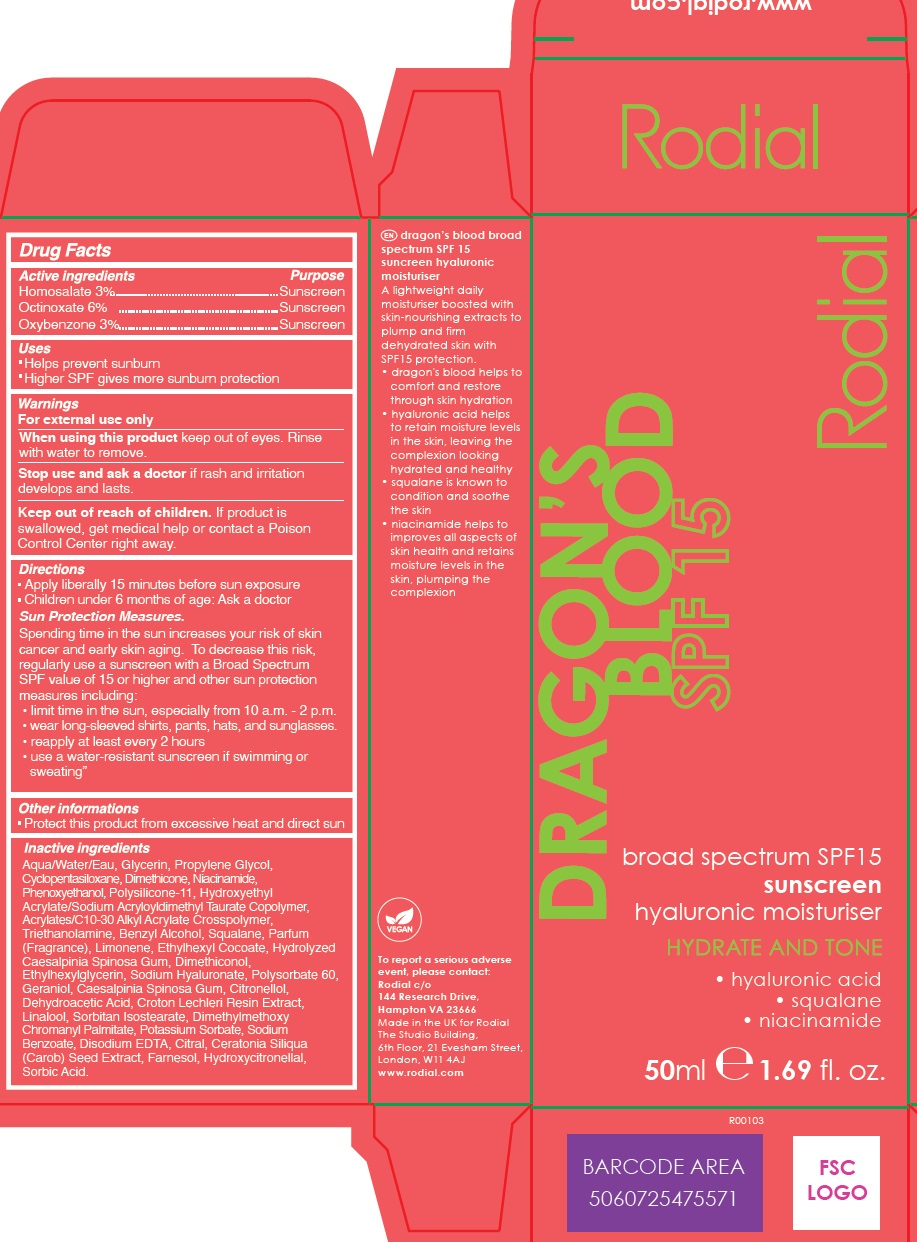 DRUG LABEL: Dragons Blood SPF15
NDC: 52456-025 | Form: CREAM
Manufacturer: Rodial
Category: otc | Type: HUMAN OTC DRUG LABEL
Date: 20240109

ACTIVE INGREDIENTS: HOMOSALATE 30 mg/1 mL; OCTINOXATE 60 mg/1 mL; OXYBENZONE 30 mg/1 mL
INACTIVE INGREDIENTS: HYALURONATE SODIUM; POLYSORBATE 60; GERANIOL; CAESALPINIA SPINOSA RESIN; .BETA.-CITRONELLOL, (R)-; DEHYDROACETIC ACID; CROTON LECHLERI RESIN; LINALOOL, (+/-)-; SORBITAN ISOSTEARATE; DIMETHYLMETHOXY CHROMANYL PALMITATE; POTASSIUM SORBATE; SODIUM BENZOATE; EDETATE DISODIUM ANHYDROUS; CITRAL; CAROB; FARNESOL; HYDROXYCITRONELLAL; SORBIC ACID; WATER; GLYCERIN; PROPYLENE GLYCOL; CYCLOMETHICONE 5; DIMETHICONE; NIACINAMIDE; PHENOXYETHANOL; DIMETHICONE/VINYL DIMETHICONE CROSSPOLYMER (SOFT PARTICLE); TROLAMINE; BENZYL ALCOHOL; SQUALANE; LIMONENE, (+)-; ETHYLHEXYL COCOATE; ETHYLHEXYLGLYCERIN

Dragon's Blood SPF15

Active ingredients

Homosalate 3%

Octinoxate 6%

Oxybenzone 3%

Purpose

Sunscreen

Uses

- Helps prevent sunburn
- Higher SPF gives more sunburn protection

Warnings

For external use only

When using this product

keep out of eyes. Rinse with water to remove.

Stop use and ask a doctor

if rash and irritation develops and lasts.

Keep out of reach of children.

If product is swallowed, get medical help or contact a Poison Control Center right away.

Directions

- Apply liberally 15 minutes before sun exposure
- Children under 6 months of age: Ask a doctor

Sun Protection Measures.
Spending time in the sun increases your risk of skin cancer and early skin aging. To decrease this risk, regularly use a sunscreen with a Broad Spectrum SPF value of 15 or higher and other sun protection measures including:
• limit time in the sun, especially from 10 a.m. - 2 p.m.
• wear long-sleeved shirts, pants, hats, and sunglasses.
• reapply at least every 2 hours
• use a water-resistant sunscreen if swimming or sweating”

Other informations

- Protect this product from excessive heat and direct sun

Inactive ingredients

Aqua/Water/Eau, Glycerin, Propylene Glycol, Cyclopentasiloxane, Dimethicone, Niacinamide, Phenoxyethanol, Polysilicone-11, Hydroxyethyl Acrylate/Sodium Acryloyldimethyl Taurate Copolymer, Acrylates/C10-30 Alkyl Acrylate Crosspolymer, Triethanolamine, Benzyl Alcohol, Squalane, Parfum (Fragrance), Limonene, Ethylhexyl Cocoate, Hydrolyzed Caesalpinia Spinosa Gum, Dimethiconol, Ethylhexylglycerin, Sodium Hyaluronate, Polysorbate 60, Geraniol, Caesalpinia Spinosa Gum, Citronellol, Dehydroacetic Acid, Croton Lechleri Resin Extract, Linalool, Sorbitan Isostearate, Dimethylmethoxy Chromanyl Palmitate, Potassium Sorbate, Sodium Benzoate, Disodium EDTA, Citral, Ceratonia Siliqua
(Carob) Seed Extract, Farnesol, Hydroxycitronellal, Sorbic Acid.